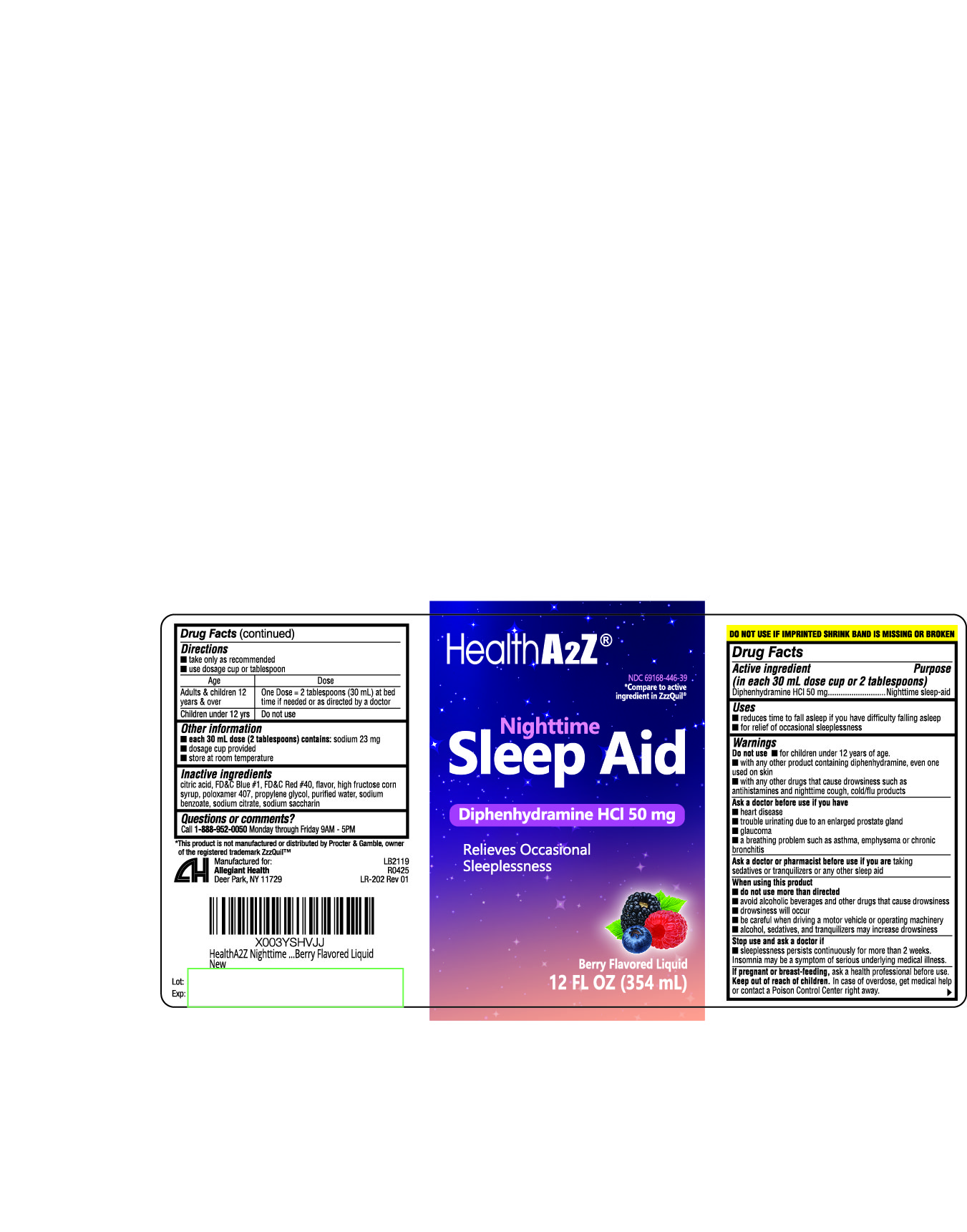 DRUG LABEL: Nighttime Sleep Aid
NDC: 69168-446 | Form: LIQUID
Manufacturer: Allegiant Health
Category: otc | Type: HUMAN OTC DRUG LABEL
Date: 20240116

ACTIVE INGREDIENTS: DIPHENHYDRAMINE HYDROCHLORIDE 50 mg/30 mL
INACTIVE INGREDIENTS: CITRIC ACID MONOHYDRATE; FD&C BLUE NO. 1; FD&C RED NO. 40; HIGH FRUCTOSE CORN SYRUP; POLOXAMER 407; PROPYLENE GLYCOL; WATER; SODIUM BENZOATE; SODIUM CITRATE; SACCHARIN

446 - Nighttime Sleep Aid

Active ingredient(s)

Diphenhydramine HCl 50mg

In each 30mL dose cup or 2 tablespoons

Purpose

Nighttime sleep-aid

Use(s)

- reduces time to fall asleep if you have difficulty falling asleep
- for relief of occasional sleeplessness

Warnings

- Do not use n for children under 12 years of age.
- with any other product containing diphenhydramine, even one used on skin
- with any other drugs that cause drowsiness such as antihistamines and nighttime cough, cold/flu products

Ask a doctor before use if

- heart disease
- trouble urinating due to an enlarged prostate gland
- glaucoma
- a breathing problem such as asthma, emphysema or chronic bronchitis

Ask a doctor or pharmacist before use if

you are taking sedatives or tranquilizers or any other sleep aid

When using this product

- do not use more than directed
- avoid alcoholic beverages and other drugs that cause drowsiness
- drowsiness will occur
- be careful when driving a motor vehicle or operating machinery
- alcohol, sedatives, and tranquilizers may increase drowsiness

Stop use and ask a doctor if

- sleeplessness persists continuously for more than 2 weeks.
  Insomnia may be a symptom of serious underlying medical illness.

If pregnant or breastfeeding,

ask a health professional before use.

Keep out of reach of children

In case of overdose, get medical help or contact a Poison Control Center right away.

Directions

- take only as recommended
- use dosage cup or tablespoon

Age Dose
Adults & children

12 years & over: One Dose = 2 tablespoons (30 mL) at bed time if needed or as directed by a doctor
Children under 12 yrs: Do not use

Other information

- each 30 mL dose (2 tablespoons) contains: sodium 23 mg
- dosage cup provided
- store at room temperature
- do not use if imprinted shrink band is missing or broken

Inactive ingredients

citric acid, FD&C Blue #1, FD&C Red #40, flavor, high fructose corn syrup,
poloxamer 407, propylene glycol, purified water, sodium benzoate, sodium
citrate, sodium saccharin

Questions/Comments

Call 1-888-952-0050 Monday through Friday 9AM to 5PM

Principal Display Panel

Nighttime Sleep Aid